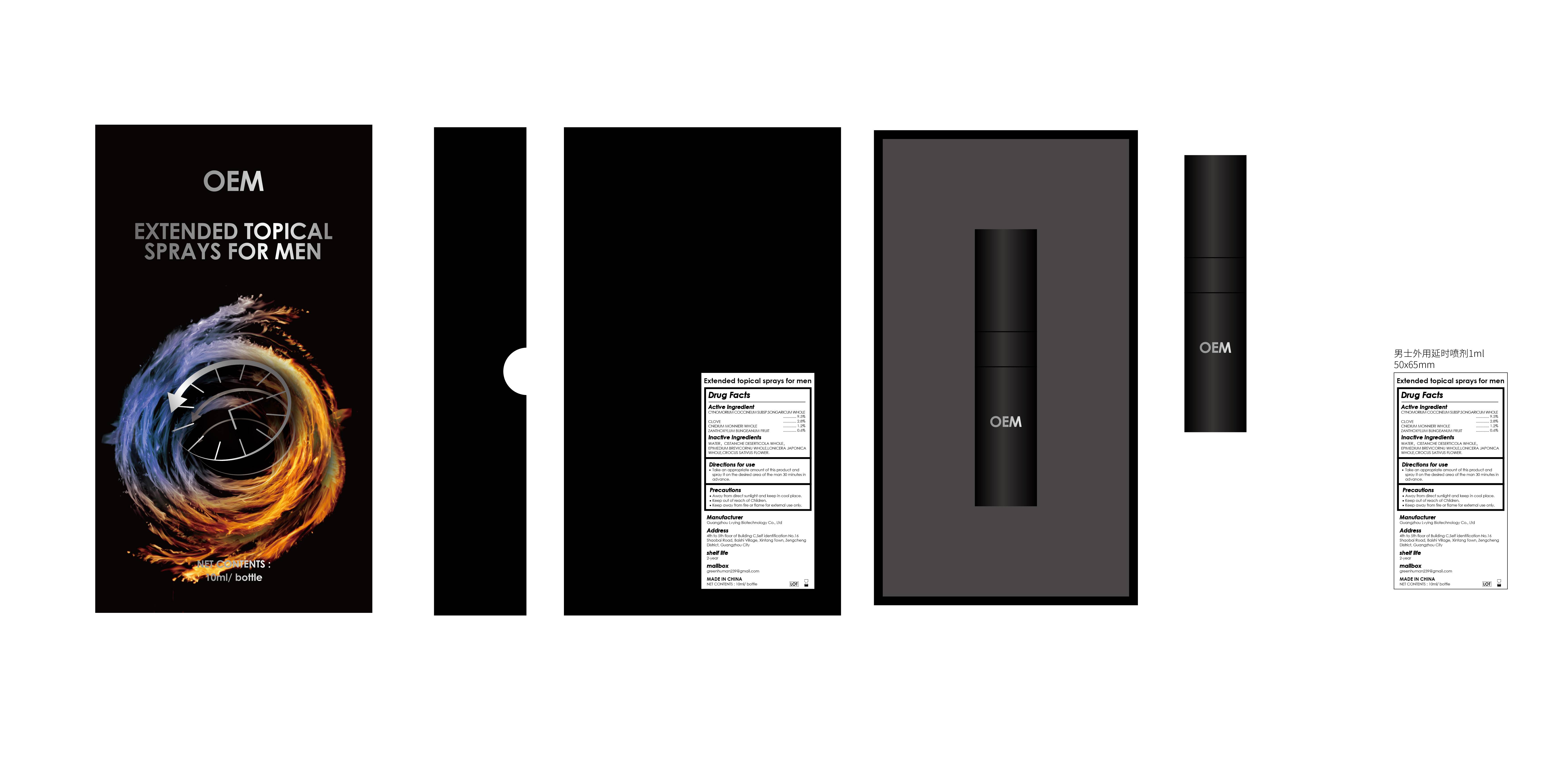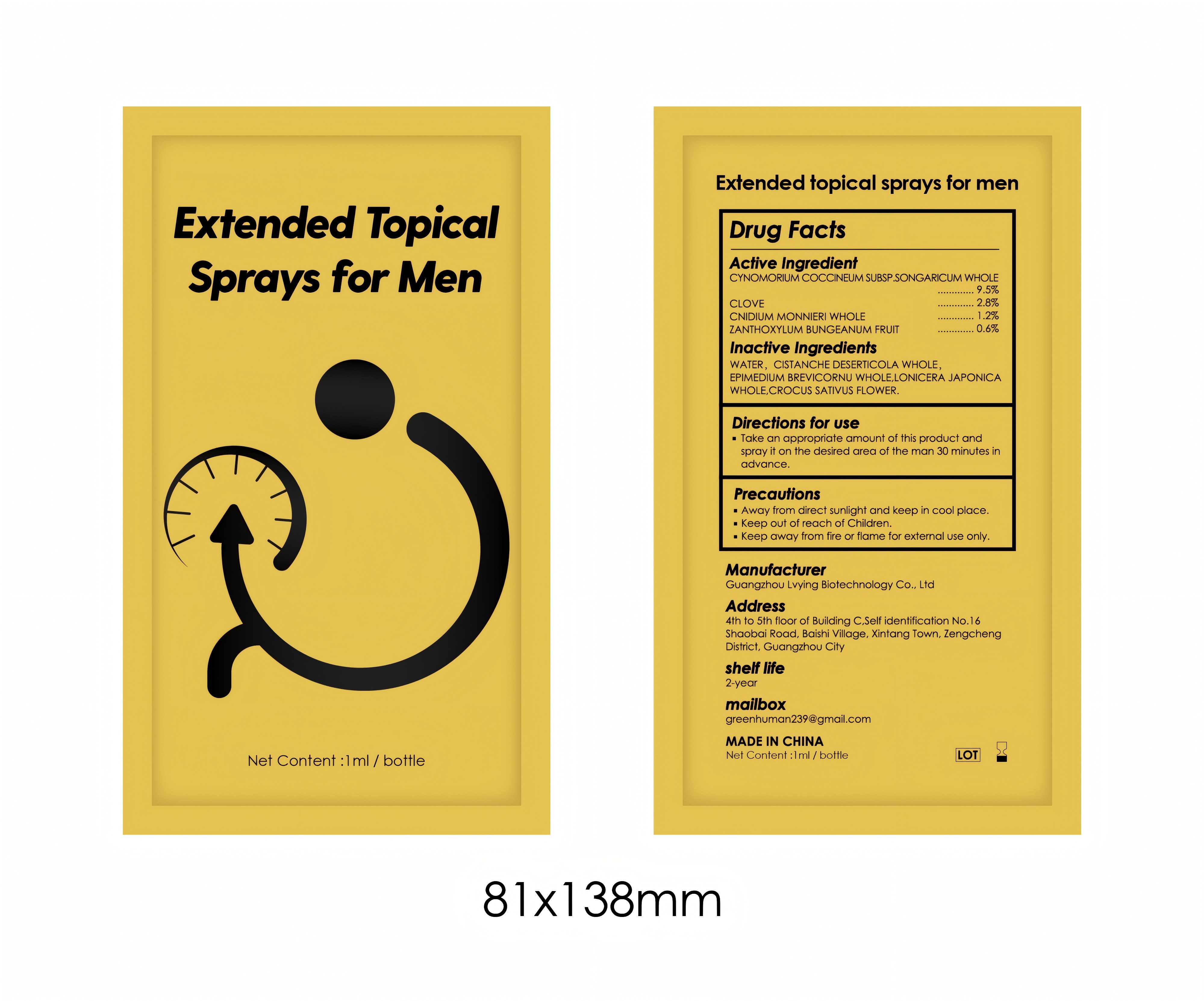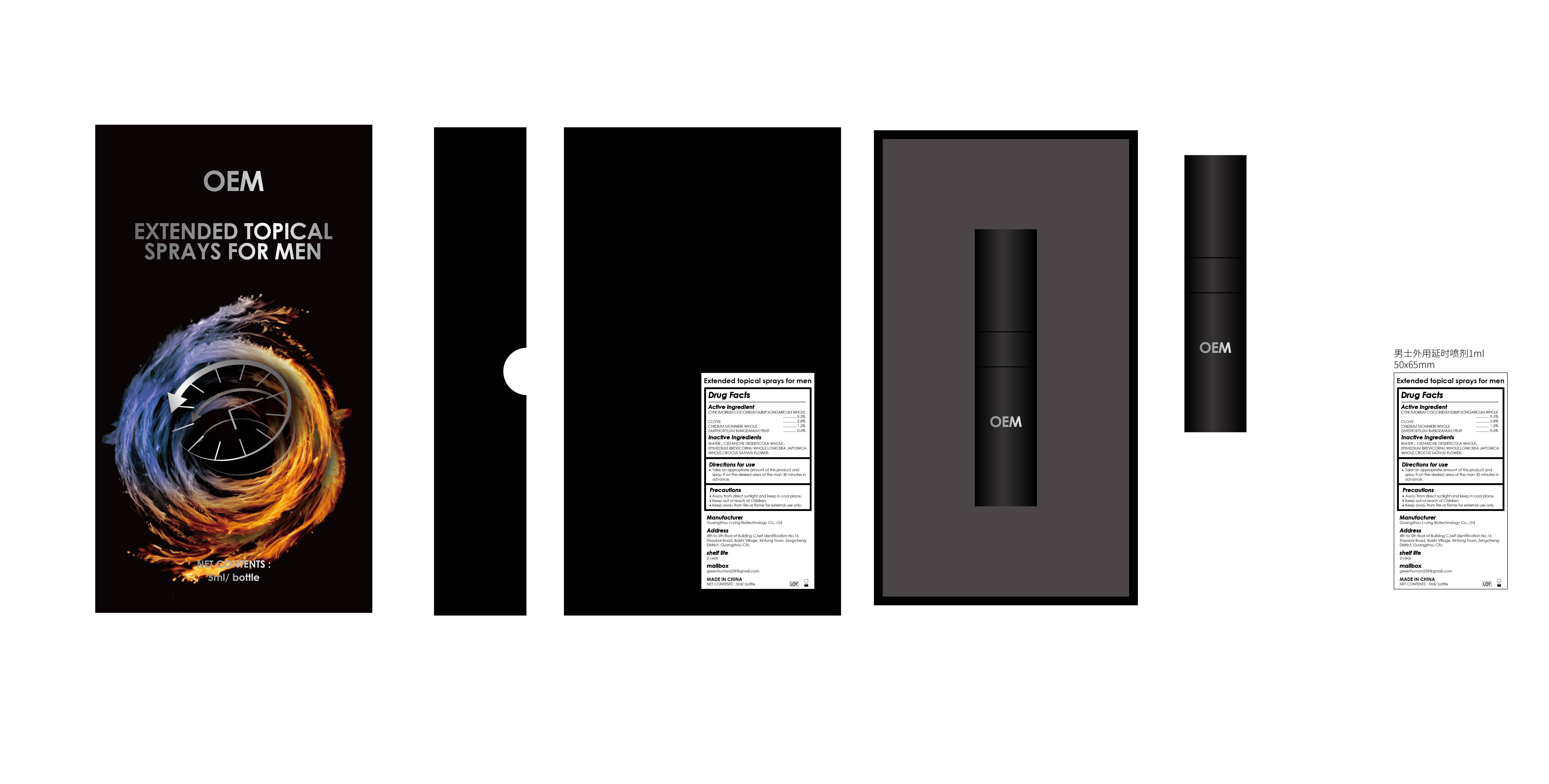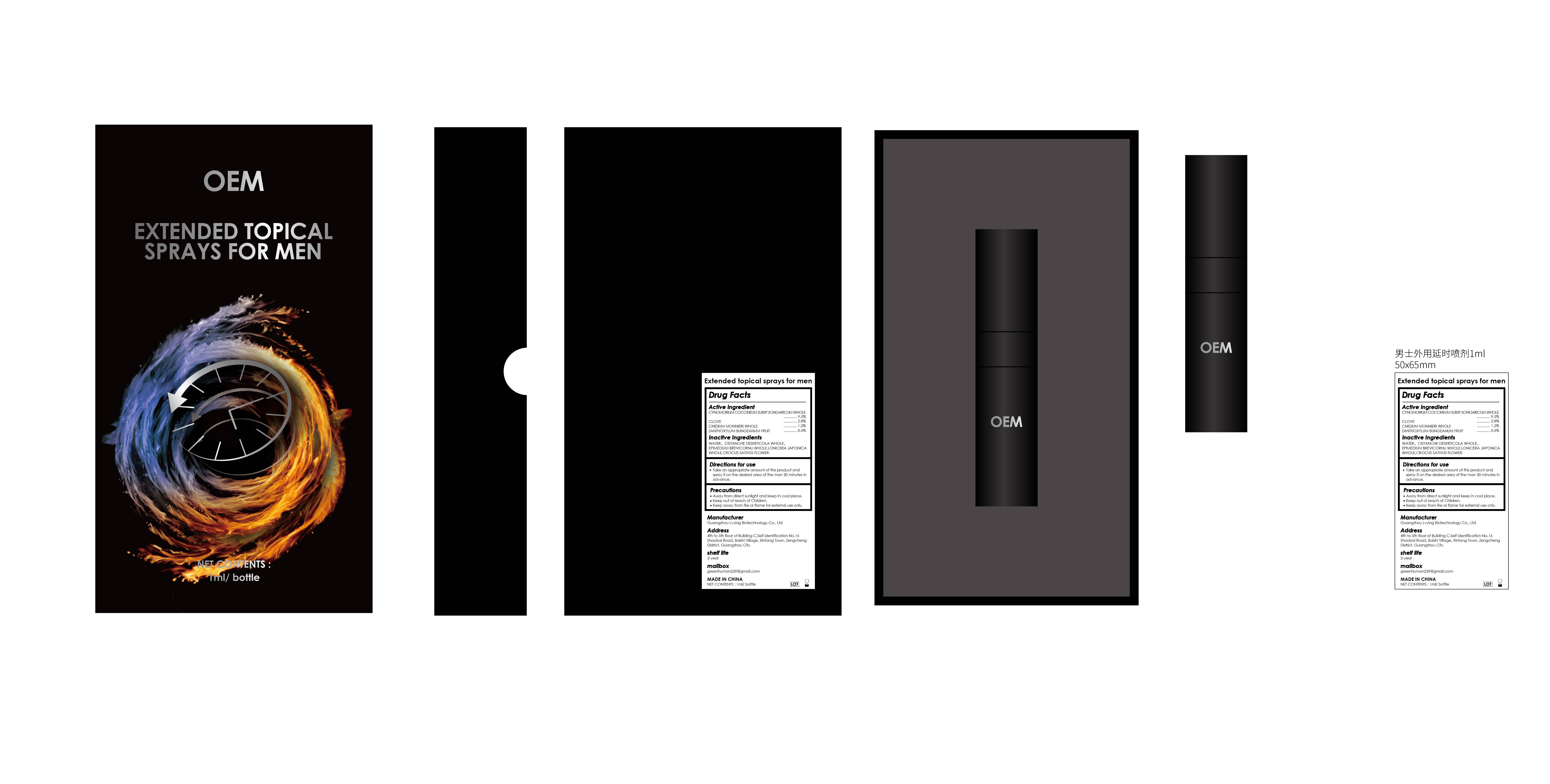 DRUG LABEL: Extended topical sprays for men
NDC: 84260-010 | Form: LIQUID
Manufacturer: Guangzhou Lvying Biotechnology Co., Ltd
Category: otc | Type: HUMAN OTC DRUG LABEL
Date: 20260130

ACTIVE INGREDIENTS: ZANTHOXYLUM BUNGEANUM FRUIT 0.6 g/100 mL; CYNOMORIUM COCCINEUM SUBSP. SONGARICUM WHOLE 9.5 g/100 mL; CLOVE 2.8 g/100 mL; CNIDIUM MONNIERI WHOLE 1.2 g/100 mL
INACTIVE INGREDIENTS: CISTANCHE DESERTICOLA WHOLE; WATER; LONICERA JAPONICA WHOLE; EPIMEDIUM BREVICORNU WHOLE; CROCUS SATIVUS FLOWER

84260-010 Extended topical sprays for men

ACTIVE INGREDIENT

CYNOMORIUM COCCINEUM SUBSP SONGARICUM WHOLE 9.5%

CLOVE 2.8%

CNIDIUM MONNIERI WHOLE 1.2%

ZANTHOXYLUM BUNGEANUM FRUIT 0.6%

PURPOSE

Extended topical sprays for men

Keep out of Reach of Children.

INDICATIONS AND USAGE

Take an appropriate amount of this product and spray it on the desired area of the man 30 minutes in advance.

WARNINGS

Keep away fom fire or flame for external use only.

DOSAGE AND ADMINISTRATION

Take an appropriate amount of this product and spray it on the desired area of the man 30 minutes in advance.

STORAGE AND HANDLING

Away from direct sunlight and keep in cool place.
Keep out of reach of Children.
Keep away from fire or flame for external use only.

INACTIVE INGREDIENT

WATER

CISTANCHE DESERTICOLA WHOLE

EPIMEDIUM BREVICORNU WHOLE

LONICERA JAPONICA WHOLE

CROCUS SATIVUS FLOWER

PACKAGE LABEL

10ml

PACKAGE LABEL

5ml/bottle

PACKAGE LABEL

1ml/bottle